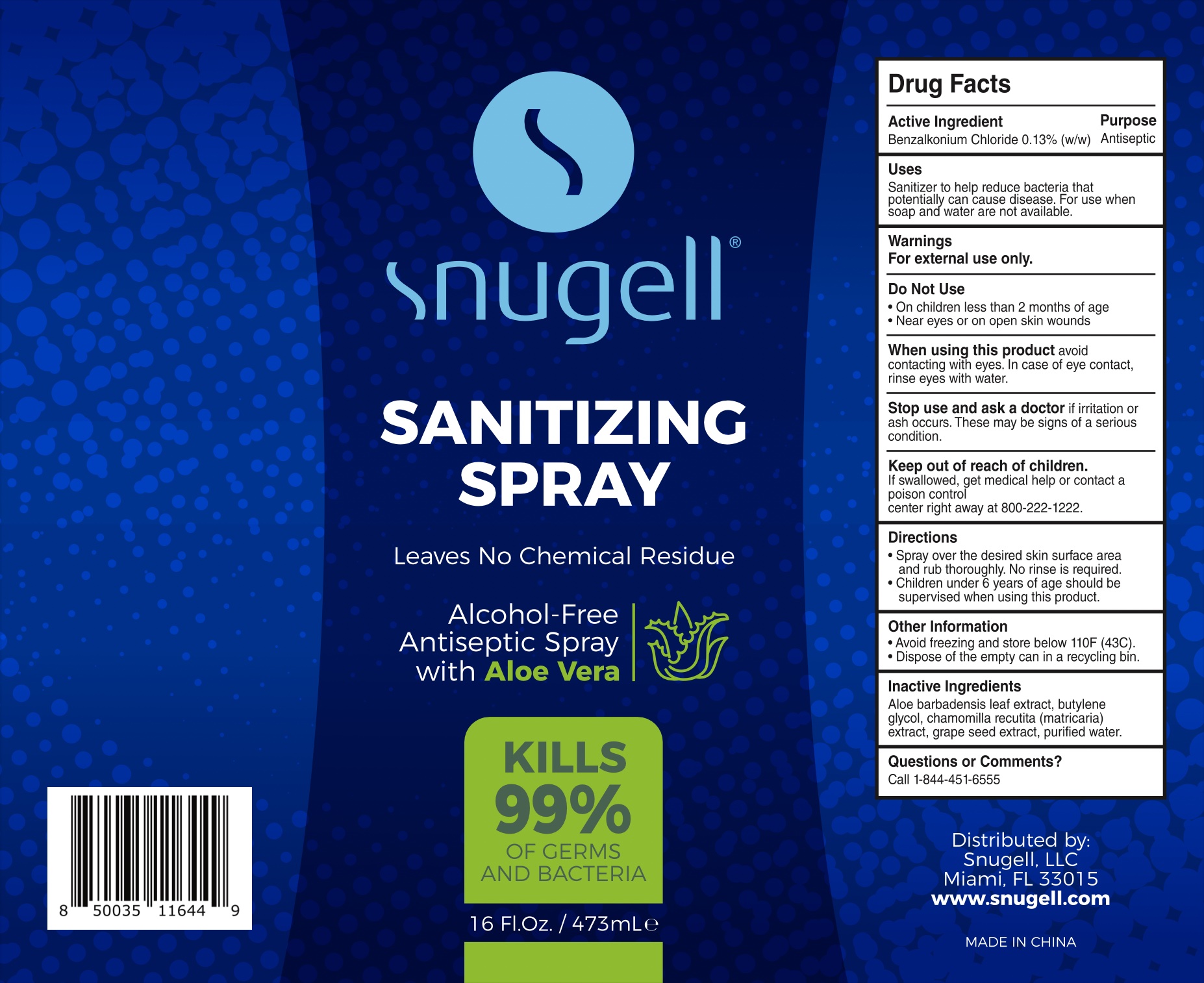 DRUG LABEL: Snugell
NDC: 82621-111 | Form: SPRAY
Manufacturer: SNUGELL LLC
Category: otc | Type: HUMAN OTC DRUG LABEL
Date: 20241213

ACTIVE INGREDIENTS: BENZALKONIUM CHLORIDE 0.13 mg/100 mL
INACTIVE INGREDIENTS: ALOE VERA LEAF; BUTYLENE GLYCOL; WATER; VITIS VINIFERA SEED; MATRICARIA CHAMOMILLA WHOLE

Snugell-QUANZHOU Spray 473 mL

Active Ingredient(s)

Benzalkonium chloride 0.13%

Purpose

Antiseptic

Use

Sanitizer to help reduce bacteria that potentially can cause disease. For use when soap and water are not available.

Warnings

For external use only.

Do not use

in children less than 2 months of age
near eyes or on open skin wounds

When using this product keep out of eyes, ears, and mouth. In case of contact with eyes, rinse eyes thoroughly with water.
Stop use and ask a doctor if irritation or rash occurs. These may be signs of a serious condition.

if swallowed, get medical help or contact a poison control center right away at 800-222-1222.

Stop use and ask a doctor if irritation or rash occurs. These may be signs of a serious condition.

Keep out of reach of children. If swallowed, get medical help or contact a Poison Control Center right away.

Directions

Spray over the desired skin surface area and rub thoroughly. No rinse is required.

Children under 6 years of age should be supervised when using this product.

QUESTIONS

Call 1-844-451-6555

Other information

.Avoid freezing and store below 110F (43 C).

Dispose the empty can in a recycle bin.

Inactive ingredients

Aloe barbadensis leaf extract, butylene glycol, chamomilla recutita (matricaria) extract, grape seed extract, purified water.

Leaves No Chemical Residue

Alcohol-Free

Antiseptic Spray

with Aloe Vera

KILLS 99% OF GERMS AND BACTERIA

Distributed by:
Snugell, LLC
Miami, FL 33015
www.snugell.com

MADE IN CHINA